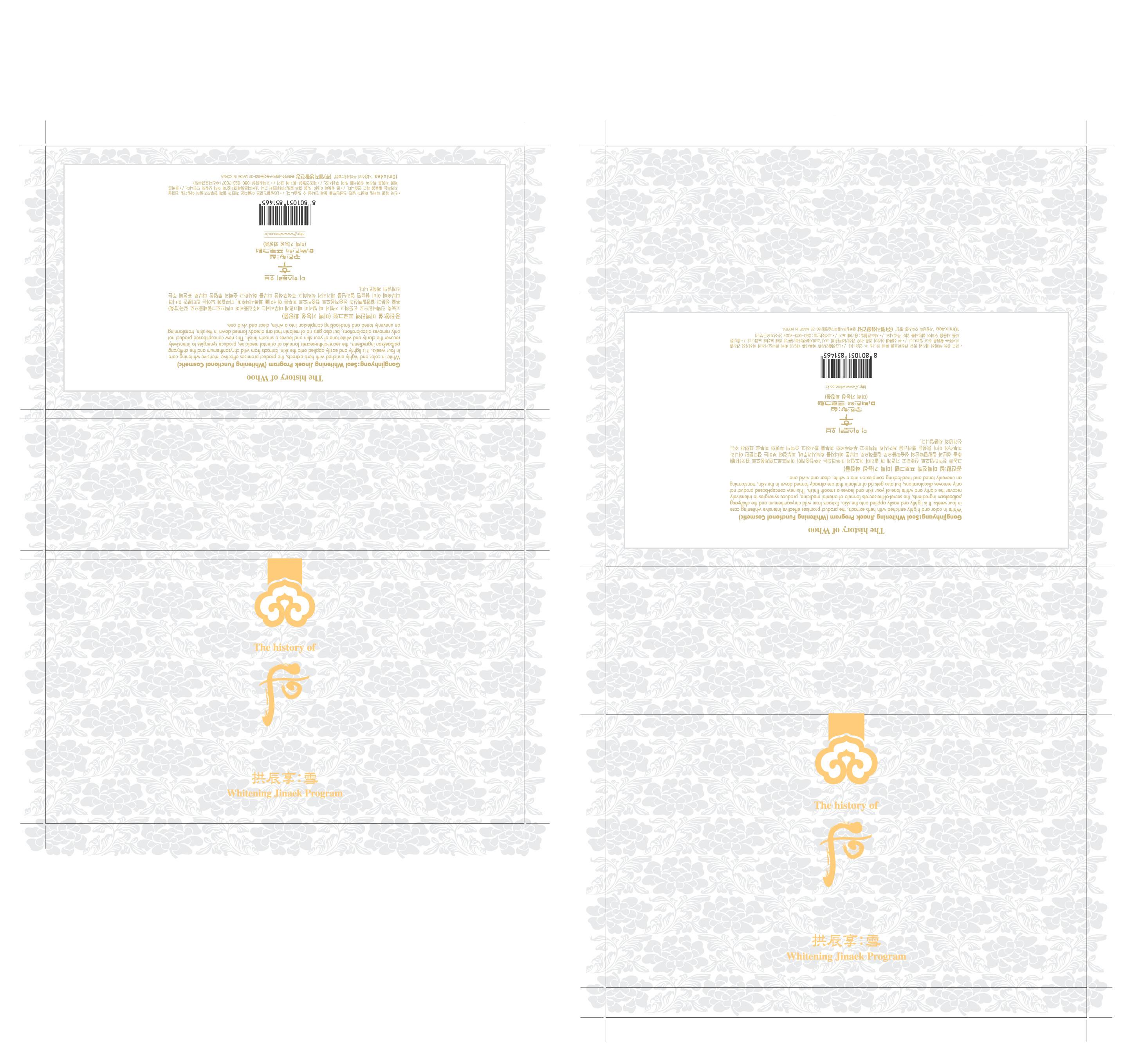 DRUG LABEL: GONGJINHYANG SEOL  WHITENING JINAEK PROGRAM
NDC: 53208-377 | Form: CREAM
Manufacturer: LG Household and Healthcare, Inc.
Category: otc | Type: HUMAN OTC DRUG LABEL
Date: 201004119

ACTIVE INGREDIENTS: DIACETYL BENZOYL LATHYROL 0.1 mL/100 mL
INACTIVE INGREDIENTS: WATER; CAPRYLIC/CAPRIC MONO/DIGLYCERIDES; CYCLOMETHICONE; DIPROPYLENE GLYCOL; DIMETHICONE; 2-ETHYLHEXANOIC ACID; PANTHENOL; GLYCERYL MONOSTEARATE; SQUALANE; POLYOXYL 40 HYDROGENATED CASTOR OIL; MORUS ALBA ROOT BARK; TITANIUM DIOXIDE; FILIPENDULA ULMARIA FLOWER; GLYCYRRHIZINATE DIPOTASSIUM; DIPROPYLENE GLYCOL; N-ACETYL-TYROSINE; TROLAMINE; EDETATE TRISODIUM; DIOSMETIN

Drug Facts

DRUG FACTS

DIACETYL BENZOYL LATHYROL 0.1mL/100mL

WARNINGS AND PRECAUTIONS

For external use only

Keep out of reach of children. Is swallowed, get medical help or contact a Poison Control Center right away.

WHEN USING

Keep out of eyes. Rinse with water to remove.

Stop use if a rash or irritation develops and lasts.

PACKAGE LABEL

The History of Whoo

Whitening Jinaek Program

INACTIVE INGREDIENT

2-ETHYLHEXANOIC ACID, CAPRYLIC/CAPRIC MONO/DIGLYCERIDES, CYCLOMETHICONE, DIMETHICONE, DIOSMETIN, DIPROPYLENE GLYCOL, EDETATE TRISODIUM, FILIPENDULA ULMARIA FLOWER, GLYCERYL MONOSTEARATE, GLYCYRRHIZINATE DIPOTASSIUM, MORUS ALBA ROOT BARK, N-ACETYL-TYROSINE, PANTHENOL, POLYOXYL 40 HYDROGENATED CASTOR OIL, SQUALANE, TITANIUM DIOXIDE, TROLAMINE, WATER